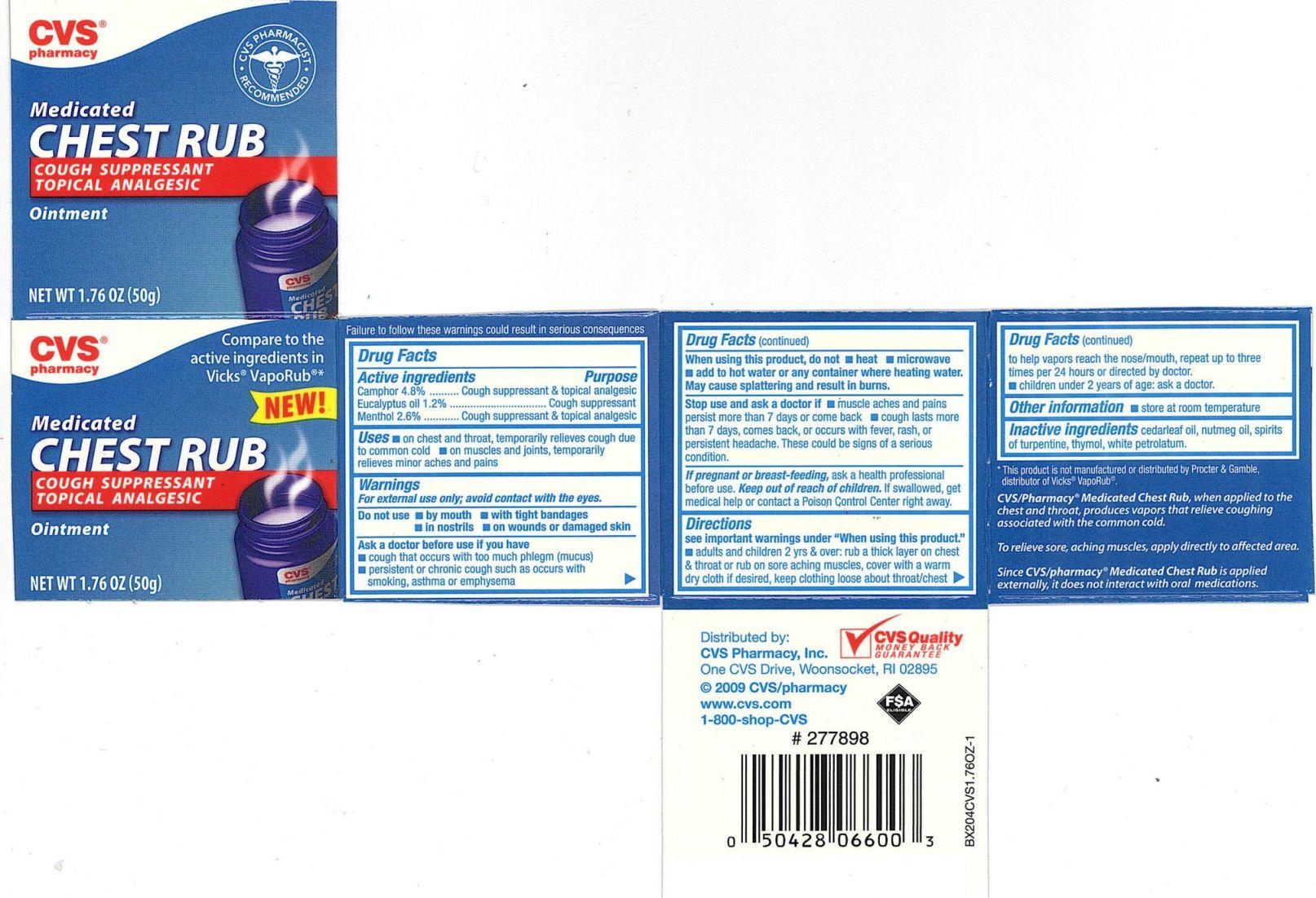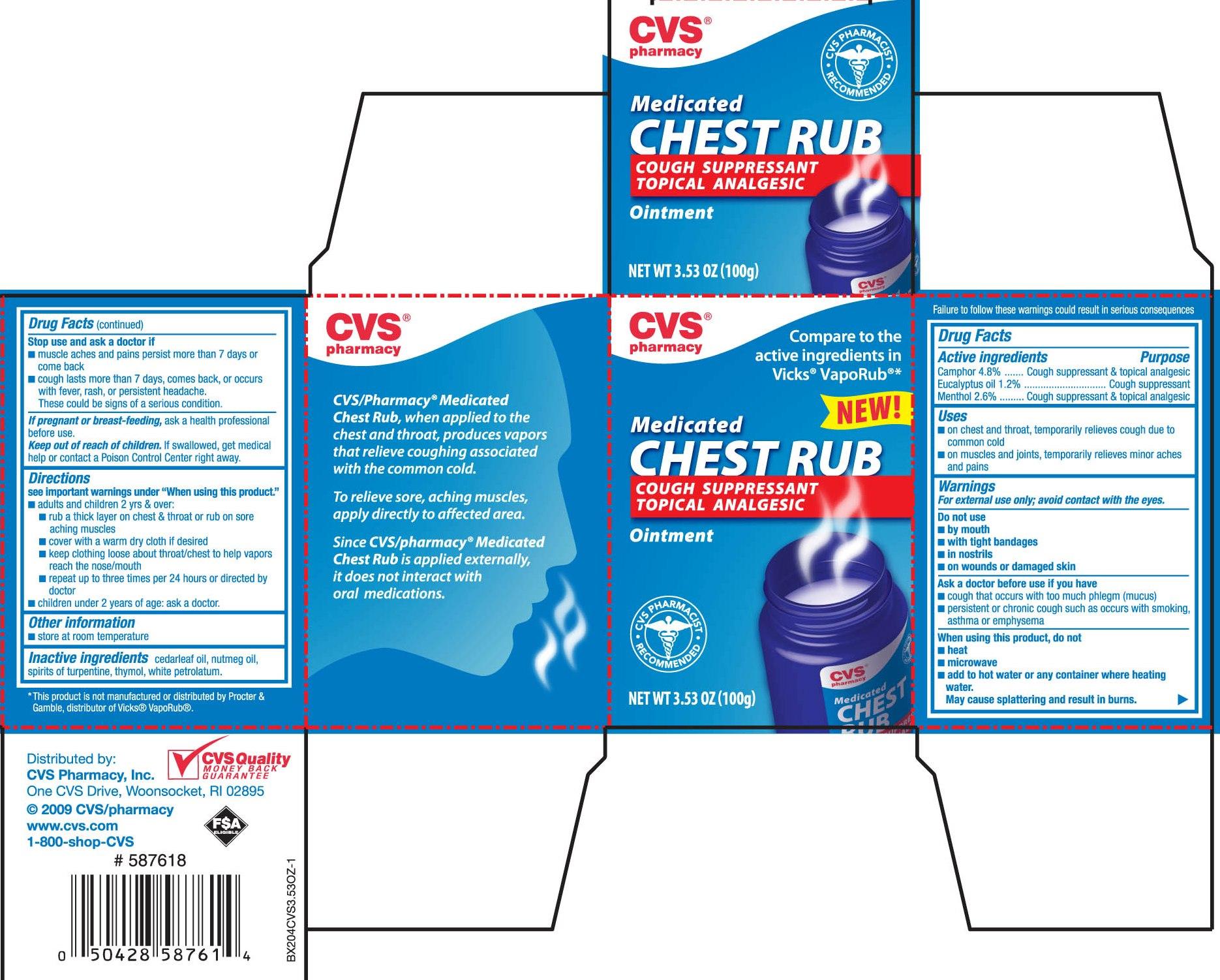 DRUG LABEL: CVS Chest Rub
NDC: 59779-057 | Form: OINTMENT
Manufacturer: CVS Pharmacy
Category: otc | Type: HUMAN OTC DRUG LABEL
Date: 20110114

ACTIVE INGREDIENTS: CAMPHOR (SYNTHETIC) 48 mg/1 g; EUCALYPTUS OIL 12 mg/1 g; MENTHOL 26 mg/1 g
INACTIVE INGREDIENTS: PETROLATUM; JUNIPERUS VIRGINIANA TWIG; TURPENTINE; THYMOL; NUTMEG OIL

DRUG FACTS

Active ingredient Purpose
Camphor 4.8%.............................................Cough suppressant and topical analgesic
Eucalyptus oil 1.2%......................................Cough suppressant
Menthol 2.6%...............................................Cough suppressant and topical analgesic

Uses
- on chest and throat, temporarily relieves cough due to common cold
- on muscles and joints, temporarily relieves minor aches and pains

Keep out of reach of children. If swallowed, get medical help or contact a
Poison Control Center right away.

Uses
- on chest and throat, temporarily relieves cough due to common cold
- on muscles and joints, temporarily relieves minor aches and pains

Warnings
For external use only; avoid contact with the eyes
Do not use - by mouth - with tight bandages
- in nostrils - on wounds or damaged skin
Ask a doctor before use if you have
- cough that occurs with too much phlegm (mucus)
- Persistent or chronic cough such as occurs with smoking, asthma or emphysema
When using this product, do not - heat - microwave - add to hot water
or any container where heating water . May cause splattering and result in burns.
Stop use and ask a doctor if - muscles aches and pains persist more than 7 days or come back
- cough lasts more then 7 days, comes back, or occurs with fever, rash, or persistent headache.
These could be signs of a serious condition.
If pregnant or breast-feeding, ask a health professional before use.
Keep out of reach of children.If swallowed, get medical help or contact a
Poison Control Center right away.

Directions
see important warnings under "When using this product"
- adults and children 2 years and over: rub a thick layer on chest and throat or rub on sore aching
muscles, cover with a warm dry cloth if desired, keep clothing loose about throat.chest to help vapors
reach the nose/mouth, repeat up to three times per 24 hours or directed by doctor.
- children under 2 years of age: ask a doctor
Other information store at room temperature

Inactive Ingredients
cedarleaf oil, nutmeg oil, spirits of turpentine, thymol, white petrolatum.